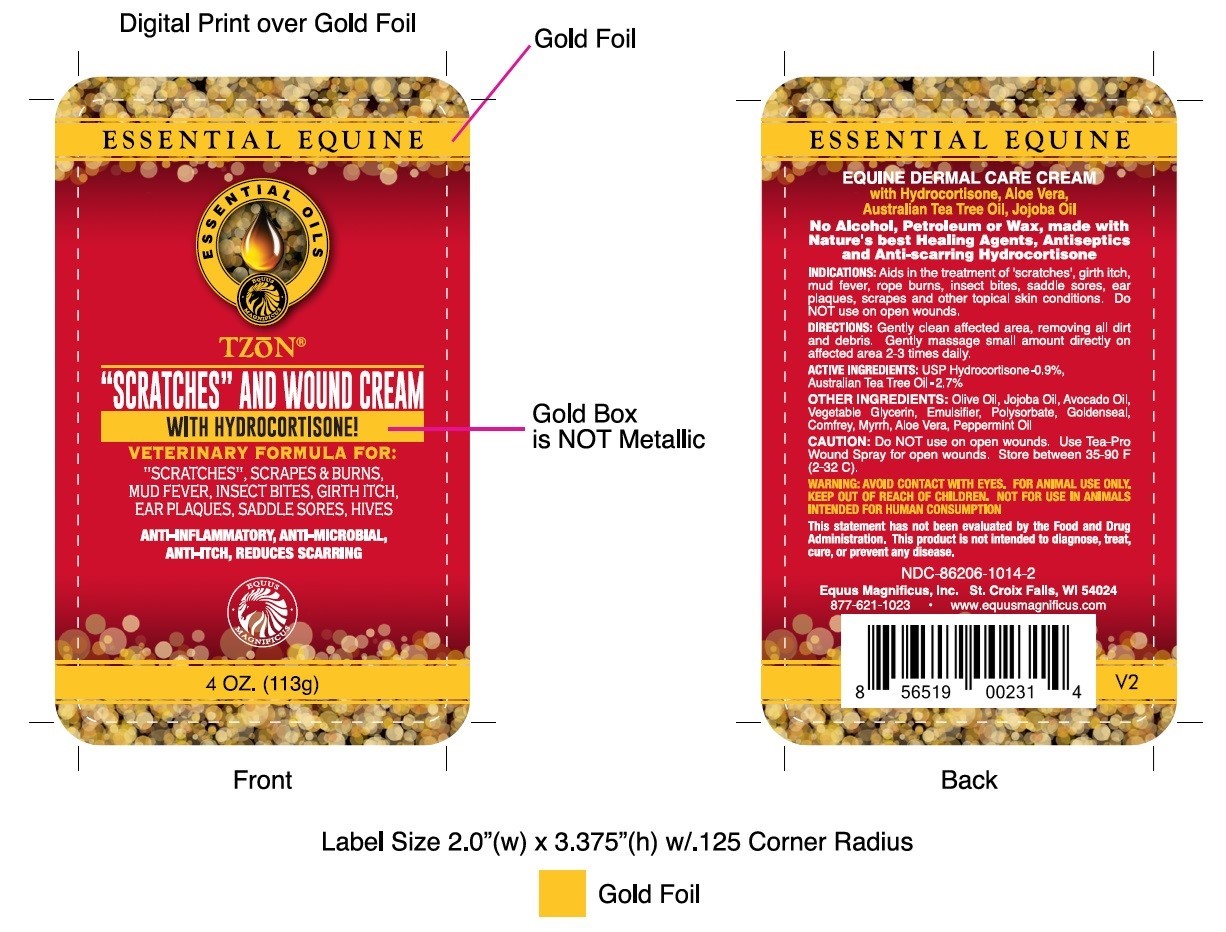 DRUG LABEL: TZoN
NDC: 86206-1014 | Form: CREAM
Manufacturer: Equus Magnificus DBA Essential Equine
Category: animal | Type: OTC ANIMAL DRUG LABEL
Date: 20251125

ACTIVE INGREDIENTS: HYDROCORTISONE 1 g/113.4 g; TEA TREE OIL 3.1 g/113.4 g
INACTIVE INGREDIENTS: HYDROXYETHYLCELLULOSE 2.6 g/113.4 g; WATER 90.1 g/113.4 g; GLYCERIN 5 g/113.4 g; MYRRH OIL 0.3 g/113.4 g; GOLDENSEAL 0.3 g/113.4 g; COMFREY 0.3 g/113.4 g; CALENDULA OFFICINALIS FLOWER 0.3 g/113.4 g; AVOCADO OIL 0.91 g/113.4 g; OLIVE OIL 1.80 g/113.4 g; JOJOBA OIL 0.91 g/113.4 g; POLYSORBATE 20 4.1 g/113.4 g; PEPPERMINT OIL 0.06 g/113.4 g; Sodium Benzoate 0.6 g/113.4 g; ALOE VERA WHOLE 0.06 g/113.4 g; GRAPEFRUIT OIL 1.9 g/113.4 g

T-ZoN 4 oz bottle

WARNINGS AND PRECAUTIONS

Caution: Do not use on open wounds.

Warning: Avoid contact with eyes. For animal use only. Keep out of reach of children. Not for use in animals intended for human consumption.